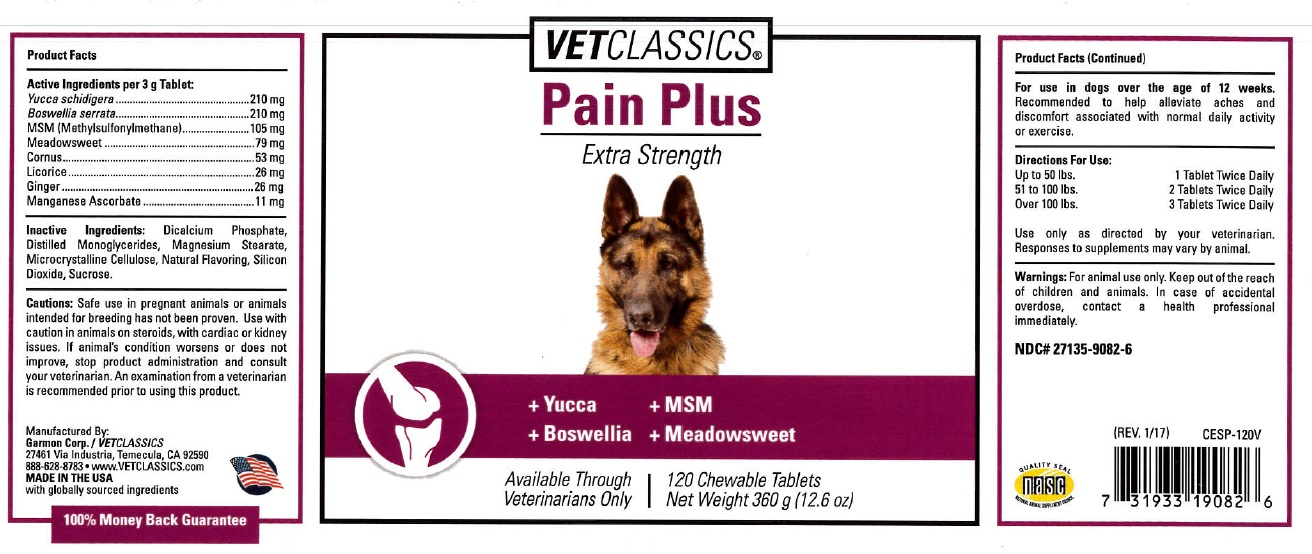 DRUG LABEL: Pain Plus Tab
NDC: 27135-9082 | Form: TABLET, CHEWABLE
Manufacturer: Garmon Corp
Category: animal | Type: OTC ANIMAL DRUG LABEL
Date: 20170512

ACTIVE INGREDIENTS: YUCCA SCHIDIGERA 210 mg/3 g; BOSWELLIA SERRATA WHOLE 210 mg/3 g; DIMETHYL SULFONE 105 mg/3 g; FILIPENDULA ULMARIA WHOLE 79 mg/3 g; CORNUS ALBA WHOLE 53 mg/3 g; LICORICE 26 mg/3 g; GINGER 26 mg/3 g; MANGANESE ASCORBATE 11 mg/3 g
INACTIVE INGREDIENTS: DIBASIC CALCIUM PHOSPHATE DIHYDRATE; DIACETYLATED MONOGLYCERIDES; MAGNESIUM STEARATE; MICROCRYSTALLINE CELLULOSE; CHICKEN; SILICON DIOXIDE; SUCROSE

Vet Classics Pain Plus

Product Facts

Active Ingredients per 3 g Tablet:

Yucca schidigera 210 mg

Boswellia serrata 210 mg

MSM (methylsulfonylmethane) 105 mg

Meadowsweet 79 mg

Cornus 53 mg

Licorice 26 mg

Ginger 26 mg

Manganese Ascorbate 11 mg

INACTIVE INGREDIENT

Inactive Ingrdients: Dicalcium Phosphate, Distilled Monoglycerides, Manganesium Stearate, Microcrystalline Cellulose, Natural flavoring, Silicon Dioxide, Sucrose.

WARNINGS AND PRECAUTIONS

Cautions: Safe use in pregnant animals or animals intended for breeding has not been proven. Use with caution in animals on steriods, with cardiac or kidney issues. If animal's condition worsens or does not improve, stop product administration and consult your veterinarian. An examination from a veterinarian is recommended prior to using this product.

Product Facts (Continued)

For use in dogs over the age of 12 weeks. Recommended to help alleviate aches and discomfort associated with normal daily activity or excercise.

DOSAGE AND ADMINISTRATION

Directions For Use:

Up to 50 lbs. 1 Tablet Twice Daily

51 to 100 lbs. 2 Tablets Twice Daily

Over 100 lbs. 3 TabletsTwice Daily

Use only as directed by your veterinarian. Responses to supplements may vary by animal.

GENERAL PRECAUTIONS

Warnings: For animal use only. Keep out of the reach of children and animals. In case of accidental overdose, contact a health professional immediately.